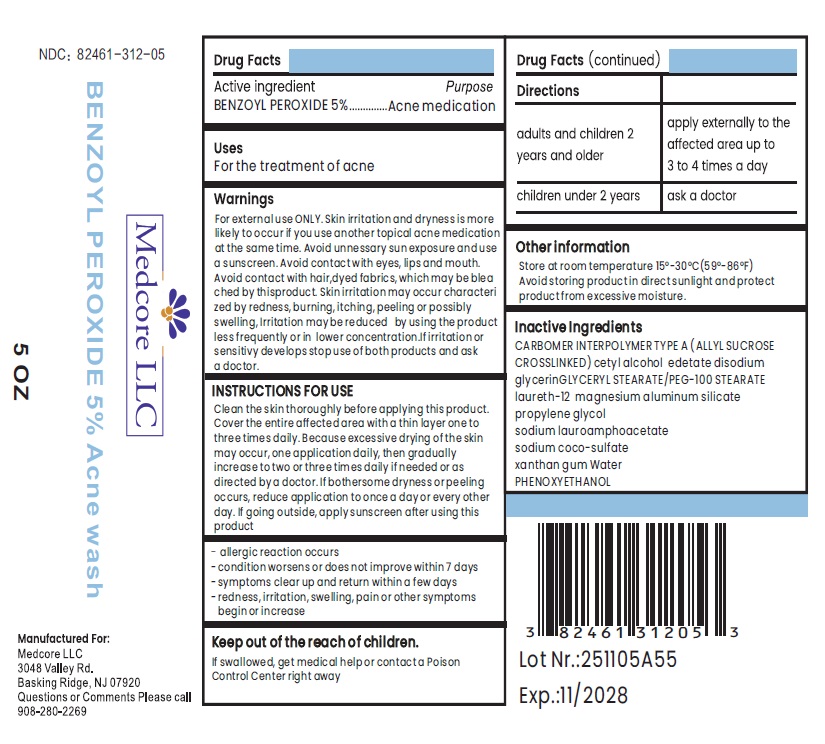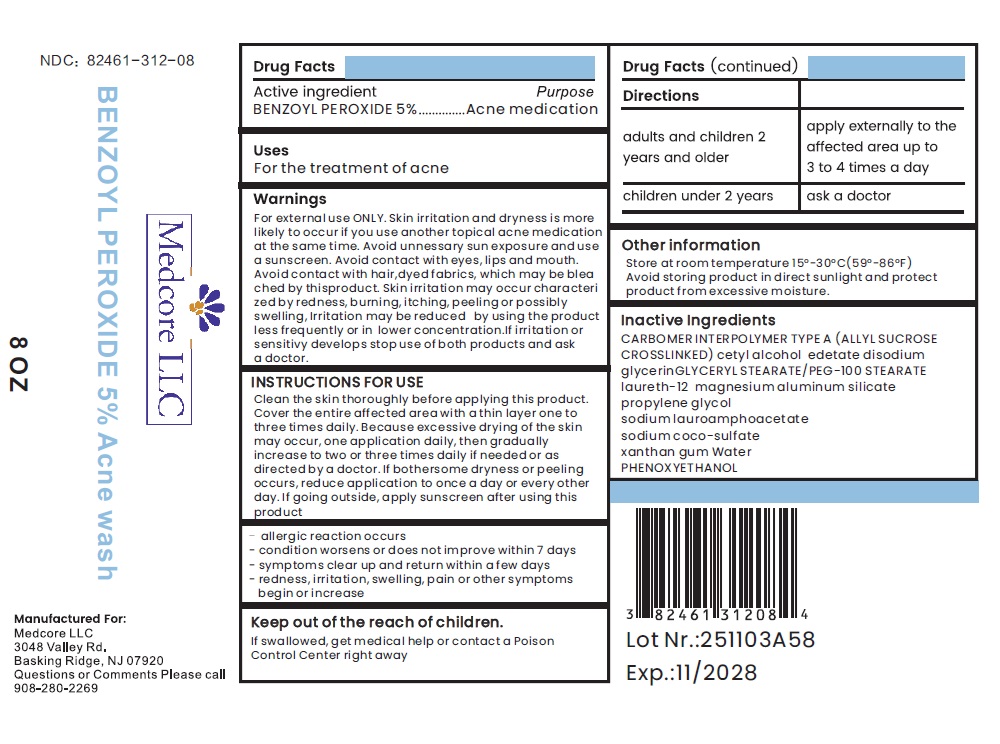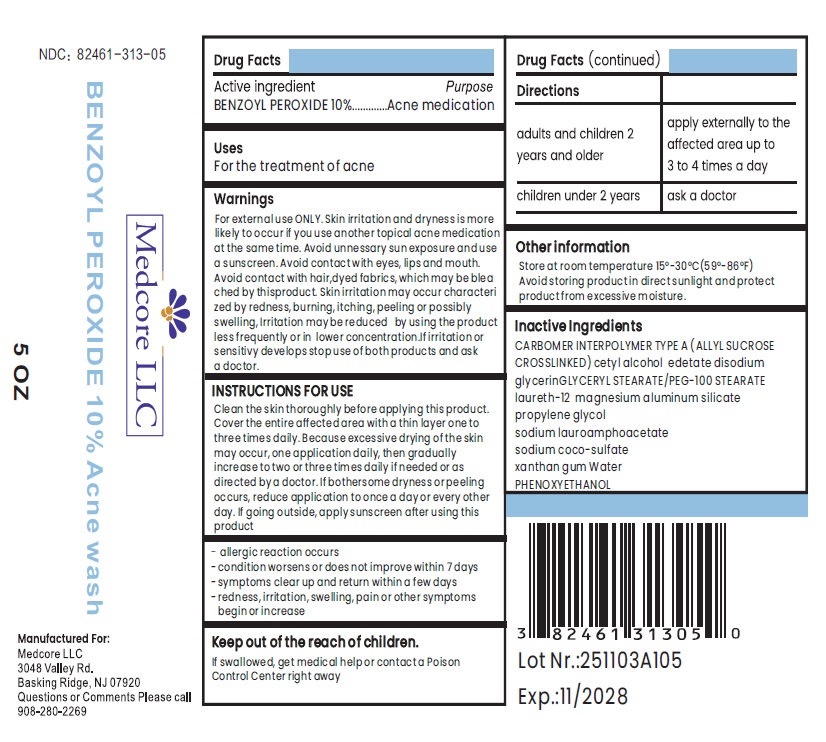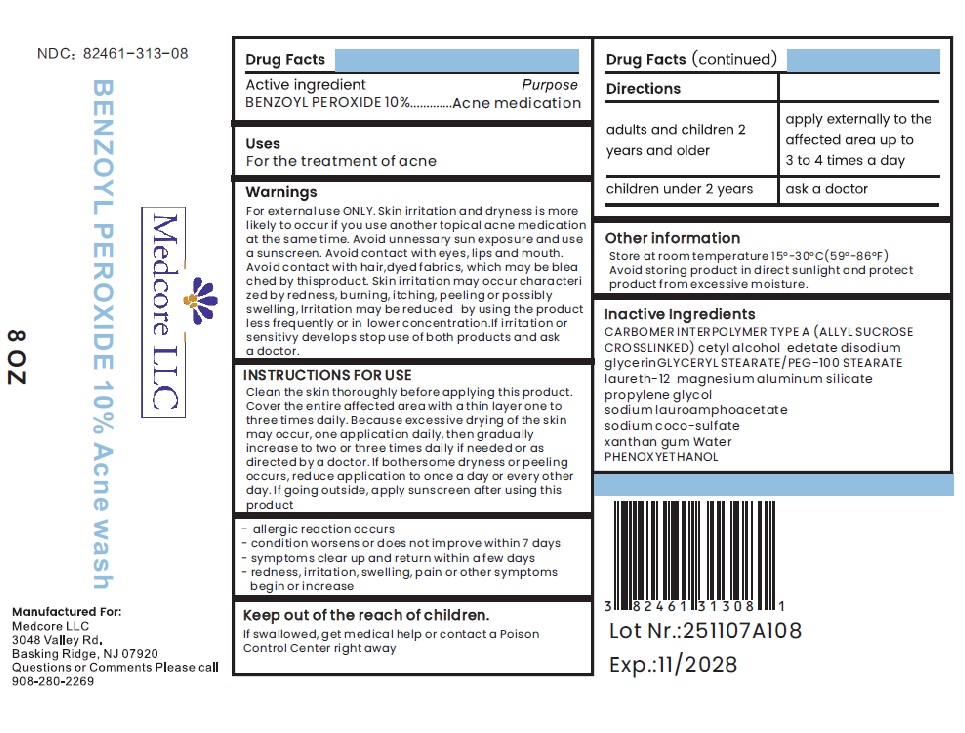 DRUG LABEL: BENZOYL PEROXIDE 5% Topical wash
NDC: 82461-312 | Form: LIQUID
Manufacturer: Medcore LLC
Category: otc | Type: HUMAN OTC DRUG LABEL
Date: 20251022

ACTIVE INGREDIENTS: BENZOYL PEROXIDE 50 mg/1 mL
INACTIVE INGREDIENTS: CARBOMER INTERPOLYMER TYPE A (ALLYL SUCROSE CROSSLINKED); CETYL ALCOHOL; EDETATE DISODIUM; GLYCERIN; GLYCERYL STEARATE/PEG-100 STEARATE; LAURETH-12; MAGNESIUM ALUMINUM SILICATE; PROPYLENE GLYCOL; SODIUM LAUROAMPHOACETATE; SODIUM COCO-SULFATE; XANTHAN GUM; WATER; PHENOXYETHANOL

Active ingredient

BENZOYL PEROXIDE 5% or 10%

Purpose

Acne medication

Uses

For the treatment of acne

Warnings

For external use ONLY. Skin irritation and dryness is more likely to occur if you use another topical acne medication at the same time. Avoid unnessary sun exposure and use a sunscreen. Avoid contact with eyes, lips and mouth. Avoid contact with hair,dyed fabrics, which may be bleached by thisproduct. Skin irritation may occur characterized by redness, burning, itching, peeling or possibly swelling, Irritation may be reduced by using the product less frequently or in lower concentration.If irritation or sensitivy develops stop use of both products and ask a doctor.

INSTRUCTIONS FOR USE

Clean the skin thoroughly before applying this product. Cover the entire affected area with a thin layer one to three times daily. Because excessive drying of the skin may occur, one application daily, then gradually increase to two or three times daily if needed or as directed by a doctor. If bothersome dryness or peeling occurs, reduce application to once a day or every other day. If going outside, apply sunscreen after using this product

DO NOT USE

- allergic reaction occurs
- condition worsens or does not improve within 7 days
- symptoms clear up and return within a few days
- redness, irritation, swelling, pain or other symptoms begin or increase

Keep out of the reach of children.

If swallowed, get medical help or contact a Poison Control Center right away

Directions

adults and children 2 years and older | apply externally to the affected area up to 3 to 4 times a day
children under 2 years | ask a doctor

Other information

Store at room temperature 15°-30°C(59°-86°F) Avoid storing product in direct sunlight and protect product from excessive moisture.

Inactive Ingredients

CARBOMER INTERPOLYMER TYPE A (ALLYL SUCROSE CROSSLINKED) cetyl alcohol edetate disodium glycerinGLYCERYL STEARATE/PEG-100 STEARATE laureth-12 magnesium aluminum silicate propylene glycol sodium lauroamphoacetate sodium coco-sulfate xanthan gum Water PHENOXYETHANOL

PRINCIPAL DISPLAY PANEL - 5% 5 OZ Bottle Label

NDC: 82461-312-05

Medcore LLC

BENZOYL PEROXIDE 5% Acne wash

5 OZ

Manufactured For:
Medcore LLC
3048 Valley Rd.
Basking Ridge, NJ 07920
Questions or Comments Please call
908-280-2269

PRINCIPAL DISPLAY PANEL - 5% 8 OZ Bottle Label

NDC: 82461-312-08

Medcore LLC

BENZOYL PEROXIDE 5% Acne wash

8 OZ

Manufactured For:
Medcore LLC
3048 Valley Rd.
Basking Ridge, NJ 07920
Questions or Comments Please call
908-280-2269

PRINCIPAL DISPLAY PANEL - 10% 5 OZ Bottle Label

NDC: 82461-313-05

Medcore LLC

BENZOYL PEROXIDE 10% Acne wash

5 OZ

Manufactured For:
Medcore LLC
3048 Valley Rd.
Basking Ridge, NJ 07920
Questions or Comments Please call
908-280-2269

PRINCIPAL DISPLAY PANEL - 10% 8 OZ Bottle Label

NDC: 82461-313-08

Medcore LLC

BENZOYL PEROXIDE 10% Acne wash

8 OZ

Manufactured For:
Medcore LLC
3048 Valley Rd.
Basking Ridge, NJ 07920
Questions or Comments Please call
908-280-2269